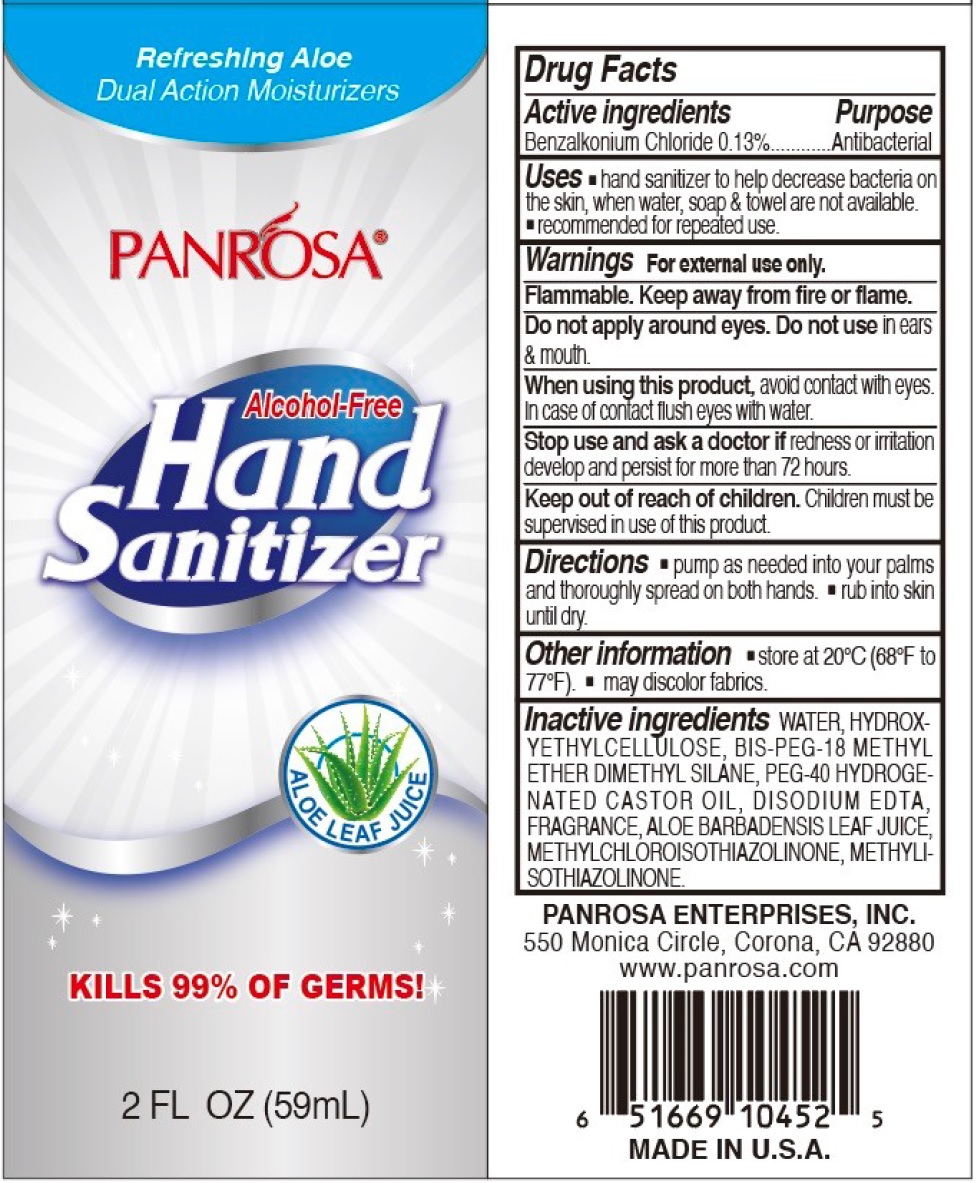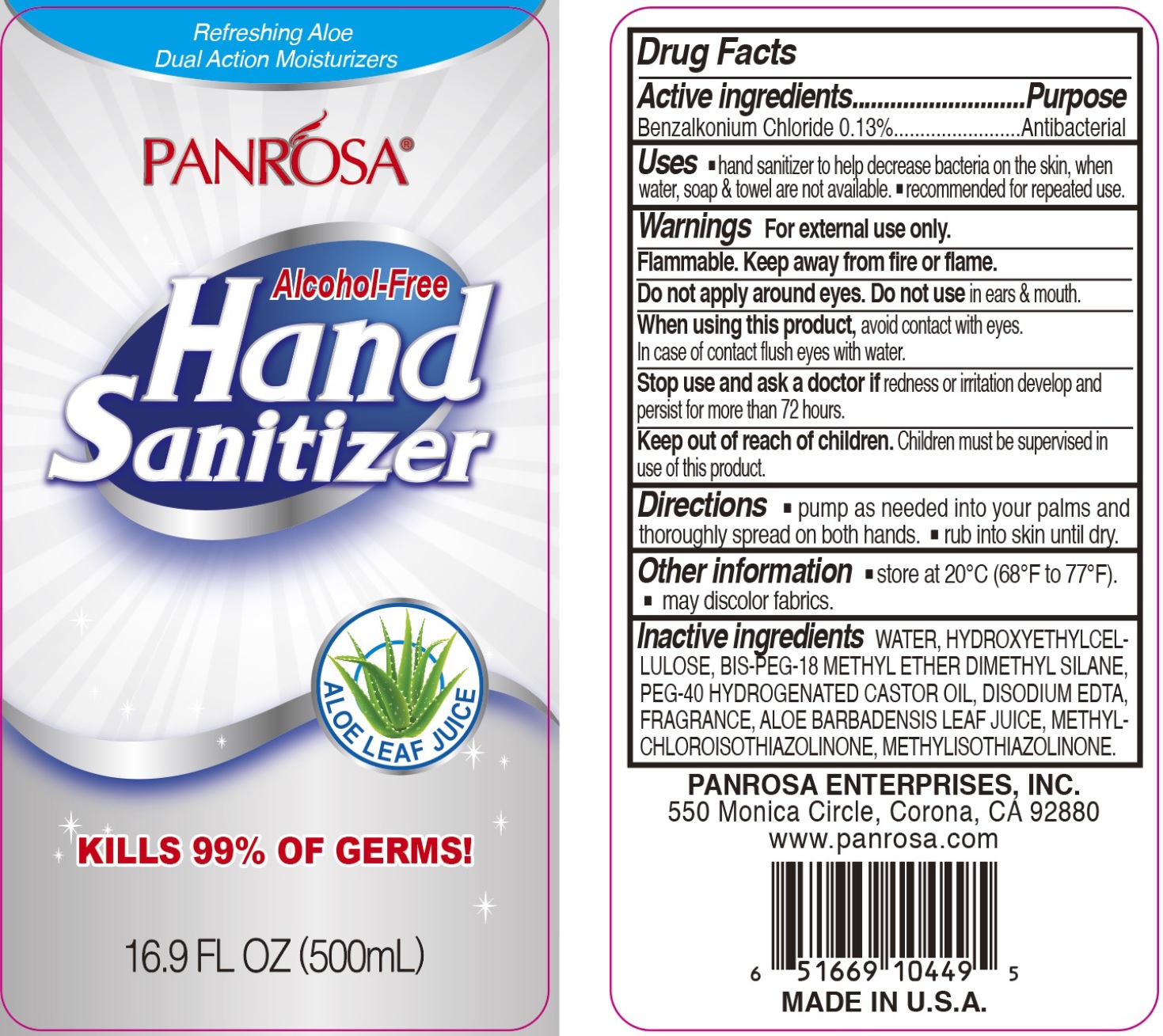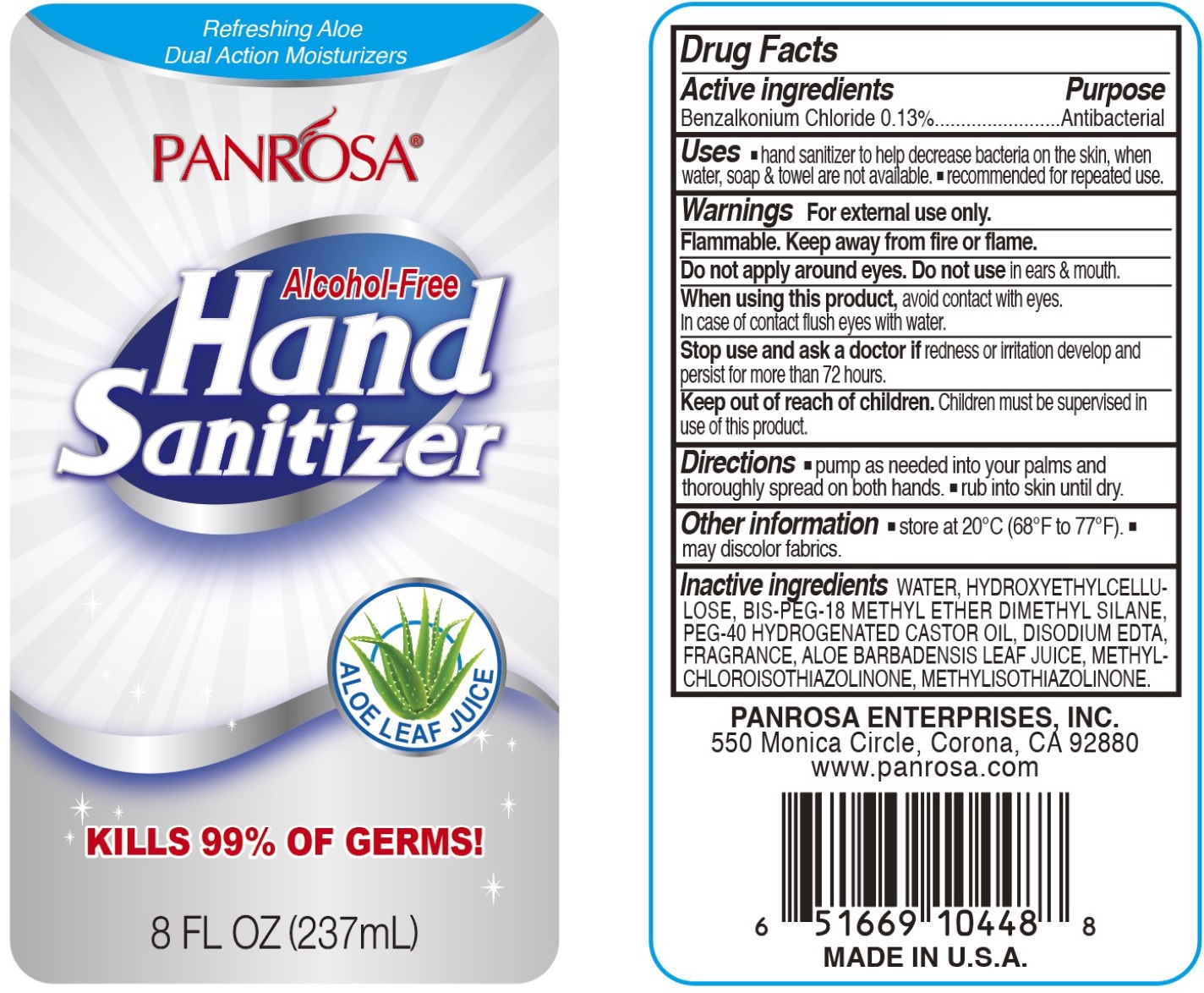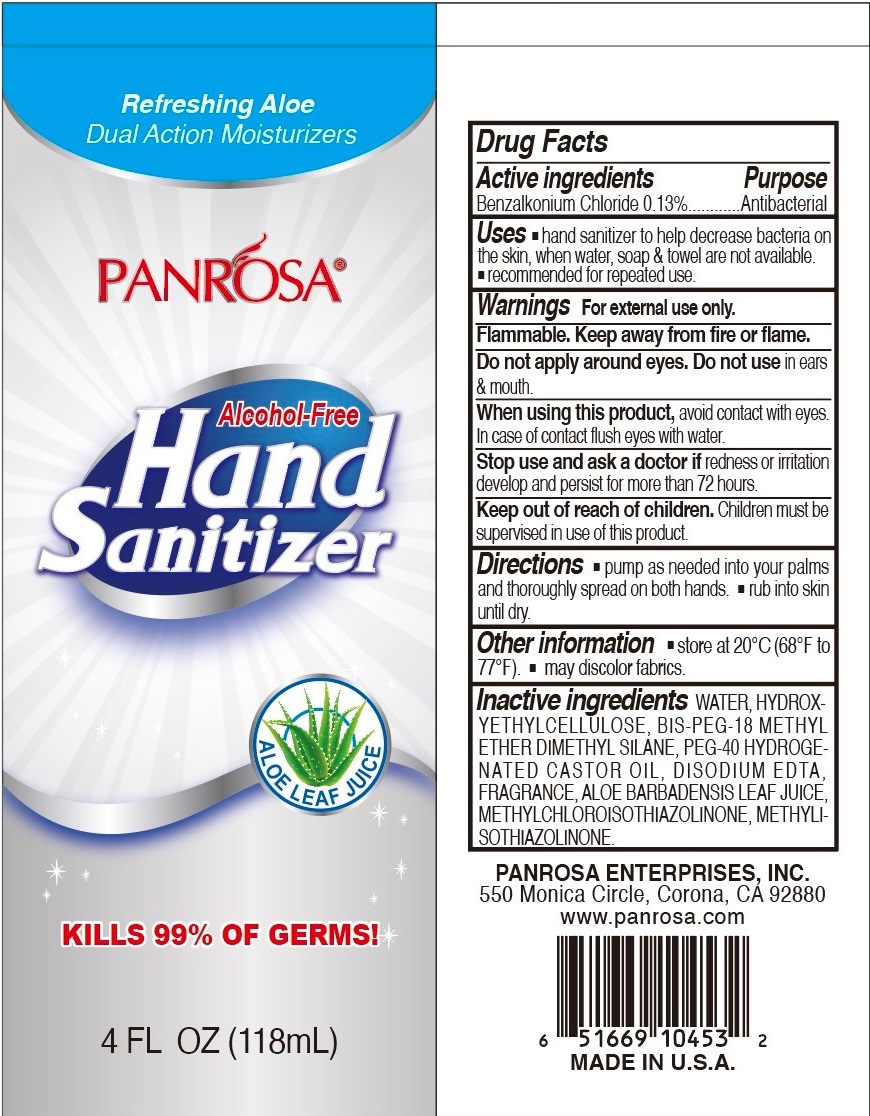 DRUG LABEL: PANROSA Alcohol-Free Hand Sanitizer with Refreshing Aloe Dual Action Moisturizers
NDC: 50302-012 | Form: GEL
Manufacturer: Panrosa Enterprises, Inc.
Category: otc | Type: HUMAN OTC DRUG LABEL
Date: 20200702

ACTIVE INGREDIENTS: BENZALKONIUM CHLORIDE 1.3 mg/1 mL
INACTIVE INGREDIENTS: WATER; HYDROXYETHYL CELLULOSE, UNSPECIFIED; BIS-PEG-18 METHYL ETHER DIMETHYL SILANE; POLYOXYL 40 HYDROGENATED CASTOR OIL; EDETATE DISODIUM ANHYDROUS; METHYLCHLOROISOTHIAZOLINONE; METHYLISOTHIAZOLINONE

PANROSA Alcohol-Free Hand Sanitizer with Refreshing Aloe Dual Action Moisturizers

Active ingredients

Benzalkonium Chloride 0.13%

Purpose

Antibacterial

Uses

- hand sanitizer to help decrease bacteria on the skin, when water, soap & towel are not available.
- recommended for repeated use.

Warnings

For external use only.

Flammable. Keep away from fire or flame.

Do not apply around eyes.

Do not use

in ears & mouth.

When using this product,

avoid contact with eyes. In case of contact flush eyes with water.

Stop use and ask a doctor if

redness or irritation develop and persist for more than 72 hours.

Keep out of reach of children.

Children must be supervised in use of this product.

Directions

- pump as needed into your palms and thoroughly spread on both hands.
- rub into skin until dry.

Other information

- store at 20°C (68°F to 77°F).
- may discolor fabrics.

Inactive ingredinets

WATER, HYDROXYETHYLCELLULOSE, BIS-PEG-18 METHYL ETHER DIMETHYL SILANE, PEG-40 HYDROGENATED CASTOR OIL, DISODIUM EDTA, FRAGRANCE, ALOE BARBADENSIS JUICE, METHYLCHLOROISOTHIAZOLINONE, METHYLISOTHIAZOLINONE.